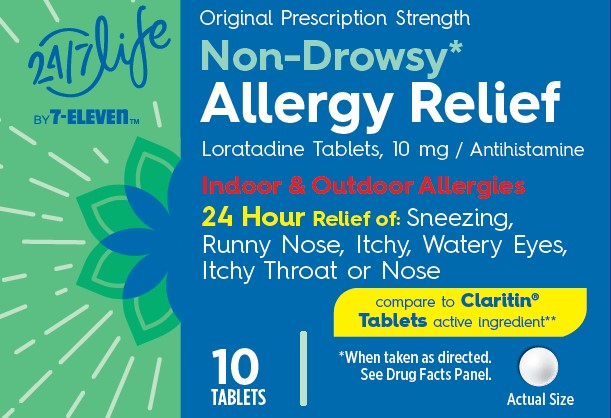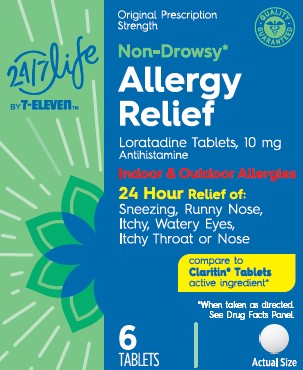 DRUG LABEL: 24 / 7 Life Non-Drowsy Allergy Relief
NDC: 29485-8156 | Form: TABLET
Manufacturer: Lil' Drug Store Products, Inc.
Category: otc | Type: HUMAN OTC DRUG LABEL
Date: 20240722

ACTIVE INGREDIENTS: LORATADINE 10 mg/1 1
INACTIVE INGREDIENTS: LACTOSE MONOHYDRATE; MAGNESIUM STEARATE; SODIUM STARCH GLYCOLATE TYPE A POTATO; CELLULOSE, MICROCRYSTALLINE

24/7 Life Non-Drowsy Allergy Relief- (7-Eleven)

Active Ingredients

Loratadine 10mg

Purpose

Antihistamine

Uses

temporarily relieves these symptoms due to hay fever or other upper respiratory allergies:

- runny nose
- itchy, watery eyes
- sneezing
- itching of the nose or throat

Warnings

Do not use

if you have ever had an allergic reaction to this product or any of its ingredients

Ask a doctor before use if you have

liver or kidney disease. Your doctor should determine if you need a different dose.

When using this product

do not take more than directed. Taking more than directed may cause drowsiness.

Stop use and ask a doctor

if an allergic reaction to this product occurs. Seek medical help right away.

If pregnant or breast-feeding,

ask a health professional before use.

Keep out of reach of children.

In case of overdose, contact a doctor or Poison Control Center (1-800-222-1222) right away.

Direction

Adults and children 6 years and over | 1 tablet daily; not more than 1 tablet in 24 hours
Children under 6 years of age | ask a doctor
Consumers with liver or kidney disease | ask a doctor

Other Information

- store between 20° to 25°C (68° to 77°F)
- protect from excessive moisture

Inactive Ingredients

lactose monohydrate, magnesium stearate, pregelatinized starch, sodium starch glycolate

Questions

1-800-351-2000 (8AM-4:30PM CST)

Satisfaction Guaranteed 1-800-255-0711

Distributed by: 7-Eleven, Inc., Irving, TX 75063 www.7-ELEVEN.com

6 Count Carton

24 / 7 Life by 7- Eleven

Original Prescription Strength

Non-Drowsy*

Allergy Relief

Loratadine Tablets, 10 mg /Antihistamine

Indoor & Outdoor Allergies

24 Hour Relief of: Sneezing,

Runny Nose, Itchy, Watery Eyes,

Itchy Throat or Nose

compare to Claritin®

Tablets active ingredient**

*When taken as directed.

See Drug Facts Panel.

6 TABLETS

[tablet image]

Actual Size

10 Count Carton

24 / 7 Life by 7- Eleven

Original Prescription Strength

Non-Drowsy*

Allergy Relief

Loratadine Tablets, 10 mg /Antihistamine

Indoor & Outdoor Allergies

24 Hour Relief of: Sneezing,

Runny Nose, Itchy, Watery Eyes,

Itchy Throat or Nose

compare to Claritin®

Tablets active ingredient**

*When taken as directed.

See Drug Facts Panel.

10 TABLETS

[tablet image]

Actual Size